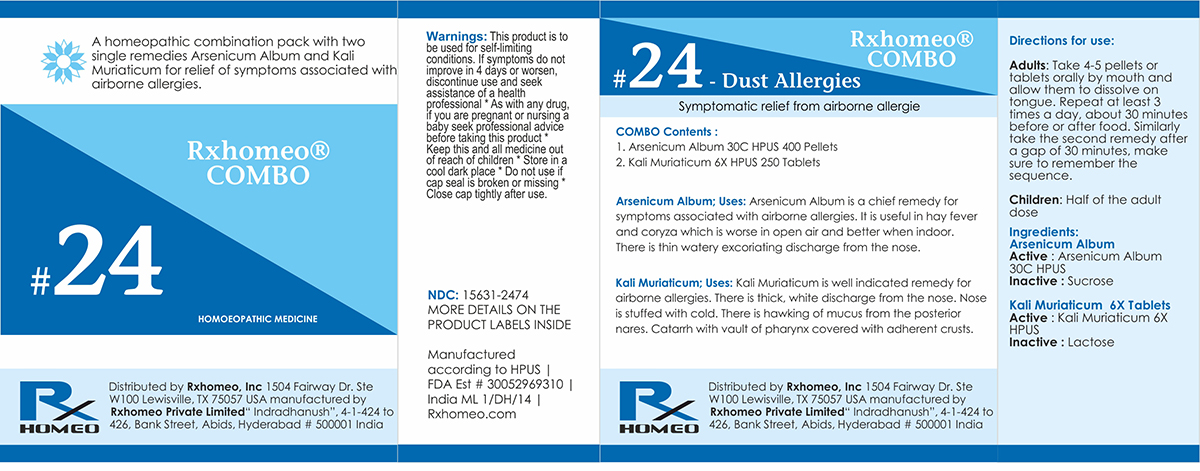 DRUG LABEL: Rxhomeo Homeopathic Combo 24
NDC: 15631-2474 | Form: KIT | Route: ORAL
Manufacturer: Rxhomeo Private Limited d.b.a.
Category: homeopathic | Type: HUMAN OTC DRUG LABEL
Date: 20161024

ACTIVE INGREDIENTS: ARSENIC TRIOXIDE 6 [hp_X]/1 1; POTASSIUM CHLORIDE 1 [hp_X]/1 1
INACTIVE INGREDIENTS: SUCROSE; LACTOSE

ACTIVE INGREDIENT

ARSENICUM ALBUM HPUS 6X and higher

KALI MURIATICUM HPUS 1X and higher

USES

A homeopathic combination pack with two single remedies Arsenicum Album and Kali Muriaticum for relief of symptoms associated with airborne allergies.

Arsenicum Album: Arsenicum Album is a chief remedy for symptoms associated with airborne allergies. It is useful in hay fever and coryza which is worse in open air and better when indoor. There is thin watery excoriating discharge from the nose.

Kali Muriaticum: Kali Muriaticum is well indicated remedy for airborne allergies. There is thick, white discharge from the nose. Nose is stuffed with cold. There is hawking of mucus from the posterior nares. Catarrh with vault of pharynx covered with adherent crusts.

INDICATIONS

Condition listed above or as directed by the physician

DOSAGE

Adults: Take 4-5 pellets or tablets orally by mouth and allow them to dissolve on tongue. Repeat at least 3 times a day, about 30 minutes before or after food. Similarly take the second remedy after a gap of 30 minutes, make sure to remember the sequence.

Children: Half of the adult dose.

WARNINGS

This product is to be used for self-limiting conditions

STOP USE

If symptoms do not improve in 4 days, or worsen, discontinue use and seek assistance of health professional

KEEP OUT OF REACH OF CHILDREN

Keep this and all medication out of reach of children

Do not use if capseal is broken or missing.

Close the cap tightly after use.

INACTIVE INGREDIENTS

Sucrose for Pellets.

Lactose for Tablets.

STORAGE

Store in a cool dark place

QUESTIONS OR COMMENTS

www.Rxhomeo.com | 1.888.2796642 | info@rxhomeo.com
Rxhomeo, Inc 1504 Fairway Dr. Ste W 100 Lewisville, TX 75057 USA